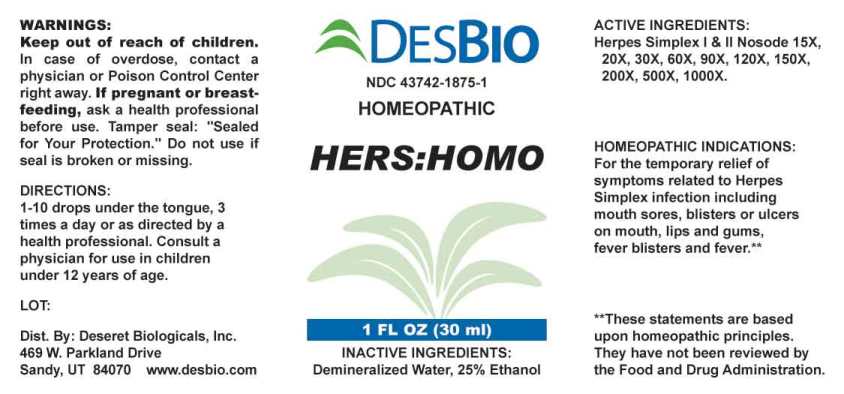 DRUG LABEL: Hers Homo
NDC: 43742-1875 | Form: LIQUID
Manufacturer: Deseret Biologicals, Inc.
Category: homeopathic | Type: HUMAN OTC DRUG LABEL
Date: 20240112

ACTIVE INGREDIENTS: HUMAN HERPESVIRUS 1 15 [hp_X]/1 mL; HUMAN HERPESVIRUS 2 15 [hp_X]/1 mL
INACTIVE INGREDIENTS: WATER; ALCOHOL

DRUG FACTS:

ACTIVE INGREDIENTS:

Herpes Simplex I 15X, 20X, 30X, 60X, 90X, 120X, 150X, 200X, 500X, 1000X, Herpes Simplex II 15X, 20X, 30X, 60X, 90X, 120X, 150X, 200X, 500X, 1000X.

HOMEOPATHIC INDICATIONS:

For the temporary relief of symptoms related to Herpes Simplex infection including mouth sores, blisters or ulcers on mouth, lips and gums, fever blisters and fever.**

**These statements are based upon homeopathic principles. They have not been reviewed by the Food and Drug Administration.

WARNINGS:

Keep out of reach of children. In case of overdose, contact a physician or Poison Control Center right away.

If pregnant or breast-feeding, ask a health professional before use.

Tamper seal: "Sealed for Your Protection." Do not use if seal is broken or missing.

Keep out of reach of children. In case of overdose, contact a physician or Poison Control Center right away.

DIRECTIONS:

1-10 drops under the tongue, 3 times a day or as directed by a health professional. Consult a physician for use in children under 12 years of age.

HOMEOPATHIC INDICATIONS:

For the temporary relief of symptoms related to Herpes Simplex infection including mouth sores, blisters or ulcers on mouth, lips and gums, fever blisters and fever.**

**These statements are based upon homeopathic principles. They have not been reviewed by the Food and Drug Administration.

INACTIVE INGREDIENTS:

Demineralized Water, 25% Ethanol

QUESTIONS:

Dist. By: Deseret Biologicals, Inc.
469 W. Parkland Drive
Sandy, UT 84070 www.desbio.com

PACKAGE LABEL DISPLAY:

DESBIO

NDC 43742-1875-1

HOMEOPATHIC

HERS: HOMO

1 FL OZ (30 ml)